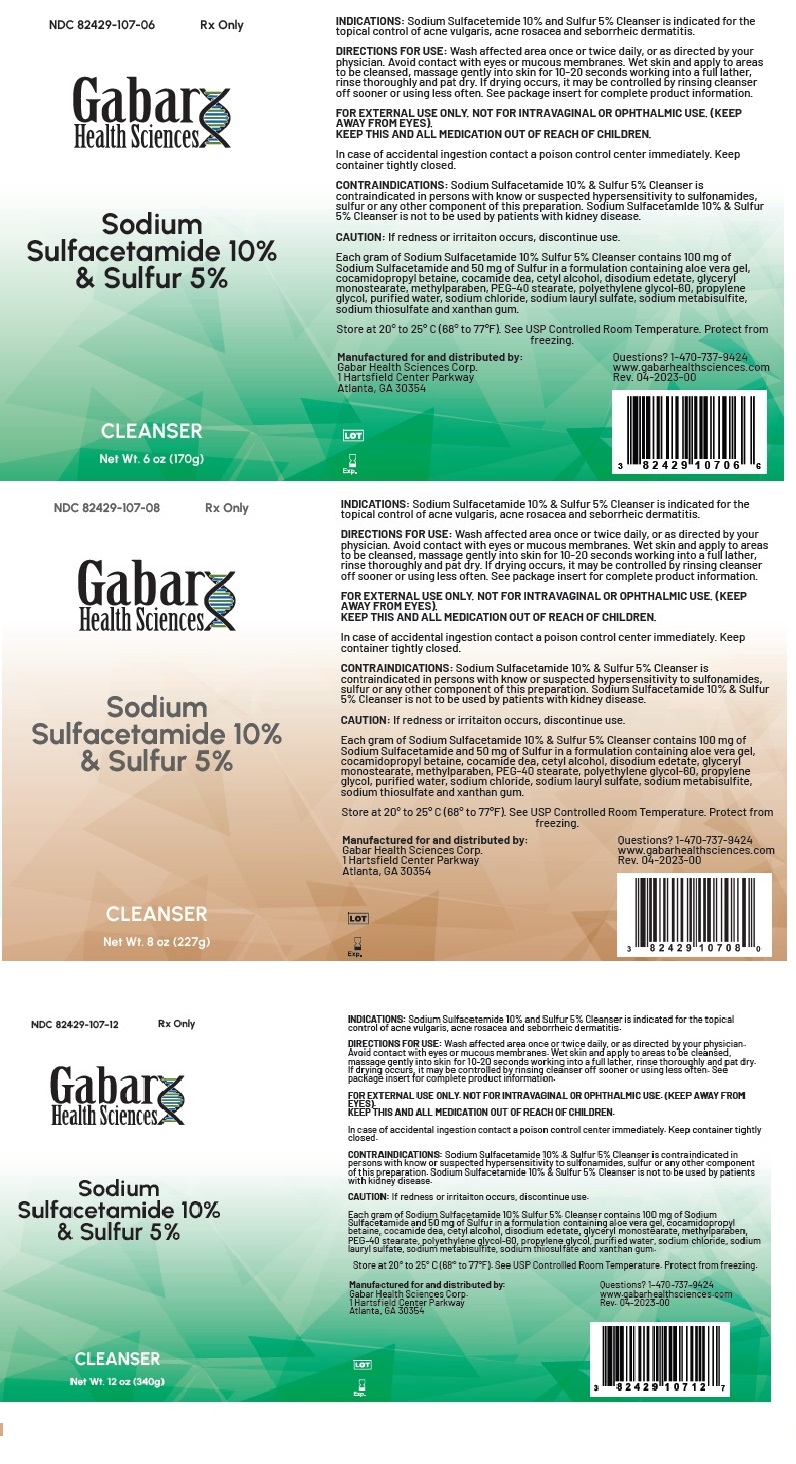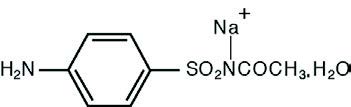 DRUG LABEL: Sodium Sulfacetamide 10% and Sulfur 5% Cleanser
NDC: 82429-107 | Form: RINSE
Manufacturer: Gabar Health Sciences Corp.
Category: prescription | Type: HUMAN PRESCRIPTION DRUG LABEL
Date: 20231021

ACTIVE INGREDIENTS: SULFACETAMIDE SODIUM 10 mg/1 g; SULFUR 5 mg/1 g
INACTIVE INGREDIENTS: ALOE VERA LEAF; BUTYLATED HYDROXYTOLUENE; CAMELLIA OLEIFERA LEAF; CETYL ALCOHOL; DISODIUM OLEAMIDO MEA-SULFOSUCCINATE; EDETATE DISODIUM; GLYCERIN; GLYCERYL MONOSTEARATE; MAGNESIUM ALUMINUM SILICATE; METHYLPARABEN; PEG-100 STEARATE; PROPYLPARABEN; WATER; SODIUM COCOYL ISETHIONATE; SODIUM METHYL COCOYL TAURATE; SODIUM THIOSULFATE; STEARYL ALCOHOL; XANTHAN GUM

Sodium Sulfacetamide 10% and Sulfur 5% Cleanser

Rx Only

DESCRIPTION

DESCRIPTION: Each gram of Sodium Sulfacetamide and Sulfur (sodium sulfacetamide 10% w/w and sulfur 5% w/w) contains 100 mg of sodium sulfacetamide and 50 mg of colloidal sulfur in a vehicle consisting of: aloe vera leaf extract, butylated hydroxytoluene, cetyl alcohol, disodium oleamido monoethanolamine sulfosuccinate, edetate disodium, fragrance, glycerin, glyceryl monostearate, magnesium aluminum silicate, methylparaben, PEG-100 stearate, propylparaben, purified water, sodium cocoyl isethionate, sodium methyl cocoyl taurate, sodium thiosulfate, stearyl alcohol, xanthan gum.

Sodium sulfacetamide is a sulfonamide with antibacterial activity while sulfur acts as a keratolytic agent. Sodium sulfacetamide is C8H9N2NaO3S·H2O with molecular weight of 254.24. Chemically, it is N-[(4-aminophenyl)sulfonyl]-acetamide, monosodium salt, monohydrate. The structural formula is:

CLINICAL PHARMACOLOGY

The most widely accepted mechanism of action of sulfonamides is the Woods-Fildes theory, which is based on the fact that sulfonamides act as competitive antagonists to para-aminobenzoic acid (PABA), an essential component for bacterial growth. While absorption through intact skin has not been determined, sodium sulfacetamide is readily absorbed from the gastrointestinal tract when taken orally and excreted in the urine, largely unchanged. The biological half-life has variously been reported as 7 to 12.8 hours.

The exact mode of action of sulfur in the treatment of acne is unknown, but it has been reported that it inhibits the growth of Propionibacterium acnes and the formation of free fatty acids.

INDICATIONS:

Sodium Sulfacetamide 10% & Sulfur 5% Cleanser is indicated in the topical control of acne vulgaris, acne rosacea and seborrheic dermatitis.

CONTRAINDICATIONS:

Sodium Sulfacetamide 10% & Sulfur 5% Cleanser is contraindicated for use by patients having known hypersensitivity to sulfonamides, sulfur, or any other component of this preparation. Sodium Sulfacetamide 10% & Sulfur 5% Cleanser is not to be used by patients with kidney disease.

WARNING

Although rare, sensitivity to sodium sulfacetamide may occur. Therefore, caution and careful supervision should be observed when prescribing this drug for patients who may be prone to hypersensitivity to topical sulfonamides. Systemic toxic reactions such as agranulocytosis, acute hemolytic anemia, purpura hemorrhagica, drug fever, jaundice and contact dermatitis indicate hypersensitivity to sulfonamides. Particular caution should be employed if areas of denuded or abraded skin are involved.

Sulfonamides are known to cause Stevens-Johnson syndrome in hypersensitive individuals. Stevens- Johnson syndrome also has been reported following the use of sodium sulfacetamide topically. Cases of drug induced systemic lupus erythematosus from topical sulfacetamide also have been reported. In one of these cases, there was a fatal outcome. KEEP OUT OF REACH OF CHILDREN.

PRECAUTIONS

PRECAUTIONSFOR EXTERNAL USE ONLY. NOT FOR OPHTHALMIC USE

General

If irritation develops, use of this product should be discontinued and appropriate therapy instituted. Patients should be very carefully observed for possible local irritation or sensitization during long- term therapy. The object of this therapy is to achieve desquamation without irritation, but Sodium Sulfacetamide and Sulfur can cause reddening and scaling of the epidermis. These side effects are not unusual in the treatment of acne vulgaris, but patients should be cautioned about the possibility.

Carcinogenesis, Mutagenesis and Impairment of Fertility
Long-term studies in animals have not been performed to evaluate carcinogenic potential.

PREGNANCY
Category C
Animal reproduction studies have not been conducted with Sodium Sulfacetamide 9% & Sulfur 4.5% Wash. It is also not known whether Sodium Sulfacetamide 10% & Sulfur 5% Cleanser can cause fetal harm when administered to a pregnant woman or can affect reproduction capacity. Sodium Sulfacetamide 10% & Sulfur 5% Cleanser should be given to a pregnant woman only if clearly needed.

NURSING MOTHERS
It is not known whether Sodium Sulfacetamide is excreted in human milk following topical use of Sodium Sulfacetamide 10% & Sulfur 5% Cleanser. However, small amounts of orally administered sulfonamides have been reported to be eliminated in human milk. In view of this and because many drugs are excreted in human milk, caution should be exercised when Sodium Sulfacetamide 10% & Sulfur 5% Cleanser is administered to a nursing woman.

PEDIATRIC USE
Safety and effectiveness in children under the age of 12 has not been established.

ADVERSE REACTIONS

Although rare, sodium sulfacetamide may cause local irritation. Call your doctor for medical adviceabout side effects. To report SUSPECTED ADVERSE REACTIONS, contact the FDA at 1-800- FDA-1088 or www.fda.gov/medwatch.

DOSAGE AND ADMINISTRATION

Wash affected areas with Sodium Sulfacetamide 10%, and Sulfur 5% Cleanser one to two times daily, or as directed by your physician. Avoid contact with eyes or mucous membranes. Wet skin and liberally apply to areas to be cleansed, massage gently into skin for 10 to 20 seconds, working into a full lather, rinse thoroughly and pat dry. If drying occurs, it may be controlled by rinsing cleanser off sooner or using cleanser less often.

HOW SUPPLIED

Sodium Sulfacetamide 10% & Sulfur 5% Cleanser is supplied in an 6oz. (170g) bottle (NDC 82429-107-06), 8oz. (227g) bottle (NDC 82429-107-08) and 12oz. (340g) bottle (NDC 82429-107-12) .

Store at 20°C to 25°C (68°F to 77°F); excursions permitted between 15°C and 30°C (between 59°F and 86°F). See USP Controlled Room Temperature.

Note: Protect from freezing and excessive heat. The product may tend to darken slightly on storage. Slight discoloration does not impair the efficacy or safety of the product. Keep bottle packet tightly closed.

Occasionally, a slight yellowish discoloration may occur when an excessive amount of the product is used and comes in contact with white fabrics. This discoloration, however, presents no problem, as it is readily removed by ordinary laundering without bleaches.

Manufactured by:
Gabar Health Sciences,
Corp Atlanta, GA 30354 USA
Rev 04/23

PRINCIPAL DISPLAY PANEL - Bottle Label

Rx only
Sodium Sulfacetamide 10% & Sulfur 5% Cleanser
SHAKE WELL BEFORE USE